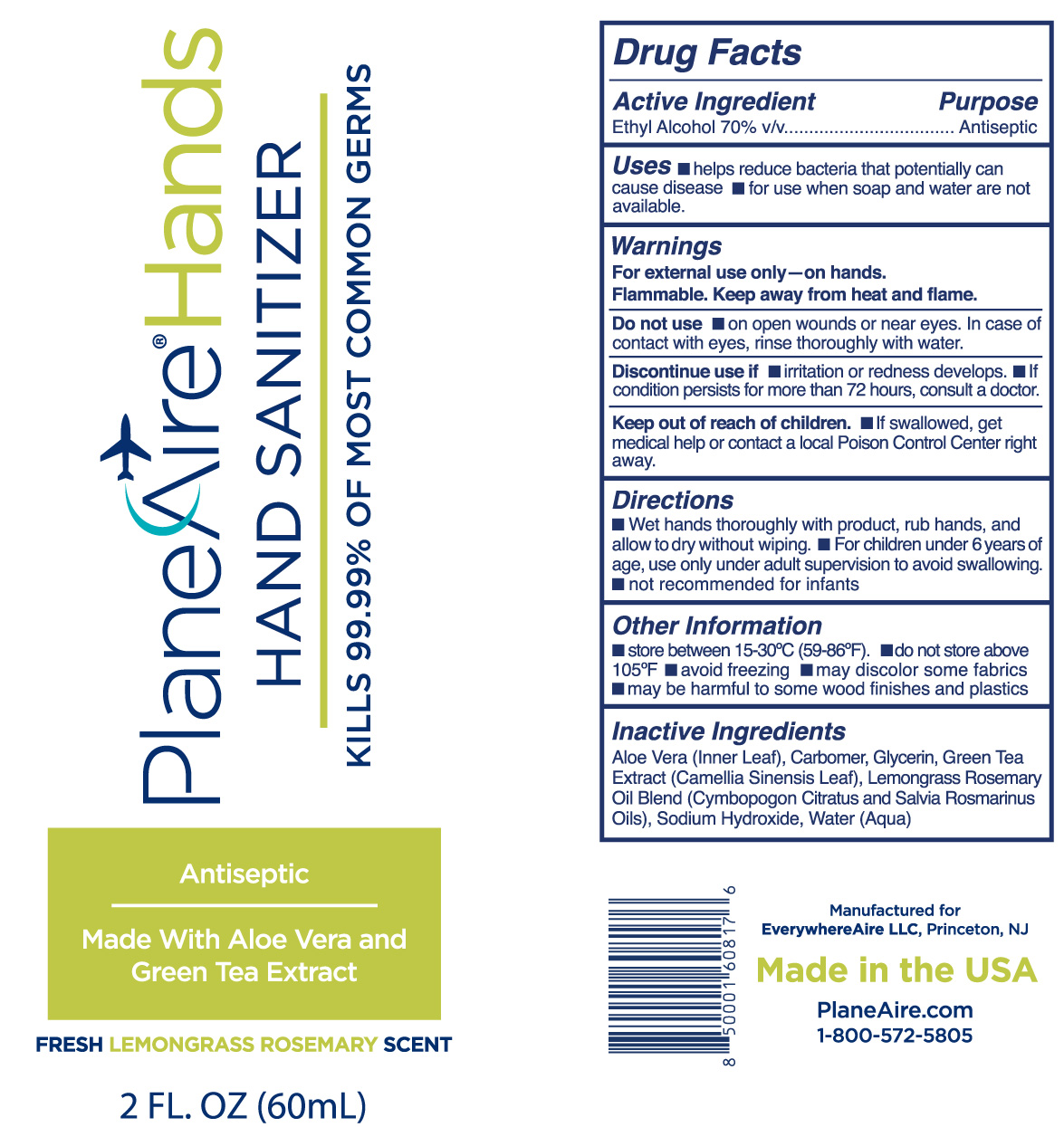 DRUG LABEL: PlaneAire Hands Hand Sanitizer
NDC: 80335-113 | Form: GEL
Manufacturer: EverywhereAire LLC
Category: otc | Type: HUMAN OTC DRUG LABEL
Date: 20211008

ACTIVE INGREDIENTS: ALCOHOL 70 mL/100 mL
INACTIVE INGREDIENTS: ROSEMARY OIL; CARBOMER 980; EAST INDIAN LEMONGRASS OIL; ALOE VERA LEAF POLYSACCHARIDES; GREEN TEA LEAF; WATER; GLYCERIN

PlaneAire Hands Lemongrass Rosemary gel aloe green tea

The hand sanitizer is manufactured using only the following ingredients in the preparation of the product (percentage in final product formulation) consistent with World Health Organization (WHO) recommendations:

1. Alcohol (ethanol) (USP or Food Chemical Codex (FCC) grade) (70%, volume/volume (v/v)) in an aqueous solution denatured according to Alcohol and Tobacco Tax and Trade Bureau regulations in 27 CFR part 20.
2. Glycerol
3. Water.
4. Other inactive ingredients.

Active Ingredient(s)

Alcohol 70% v/v.

Purpose

Antiseptic,

Use

Hand Sanitizer to help reduce bacteria that potentially can cause disease. For use when soap and water are not available.

Warnings

For external use only.- on hands. Flammable. Keep away from heat or flame

Do not use

- on open skin wounds or near eyes. In case of contact with eyes, rinse thoroughly with water

When using this product keep out of eyes, and open wounds. In case of contact with eyes, rinse eyes thoroughly with water.
Stop use if irritation or redness occurs. If condition persists for more than 72 hours, consult a doctor.
Keep out of reach of children. If swallowed, get medical help or contact a local Poison Control Center right away.

Stop use if irritation or redness occurs. If condition persists for more than 72 hours, consult a doctor.

Keep out of reach of children. If swallowed, get medical help or contact a Poison Control Center right away.

Directions

Wet hands thoroughly with product, rub hands, and allow to dry without wiping
For children under 6 years of age, use only under adult supervision to avoid swallowing
not recommended for infants

Directions

Wet hands thoroughly with product, rub hands, and allow to dry without wiping
For children under 6 years of age, use only under adult supervision to avoid swallowing
not recommended for infants

Other information

- Store between 15-30C (59-86F)
- do no store above above 105F
- avoid freezing
- may discolor some fabrics
- may be harmful to some wood finishes and plastics

Inactive ingredients

aloe vera inner leaf, green tea extract, lemongrass oil blend, rosemary oil, carbomer, glycerin, sodium hydroxide, water

Package Label - Principal Display Panel

60 mL NDC: 80335-113-02